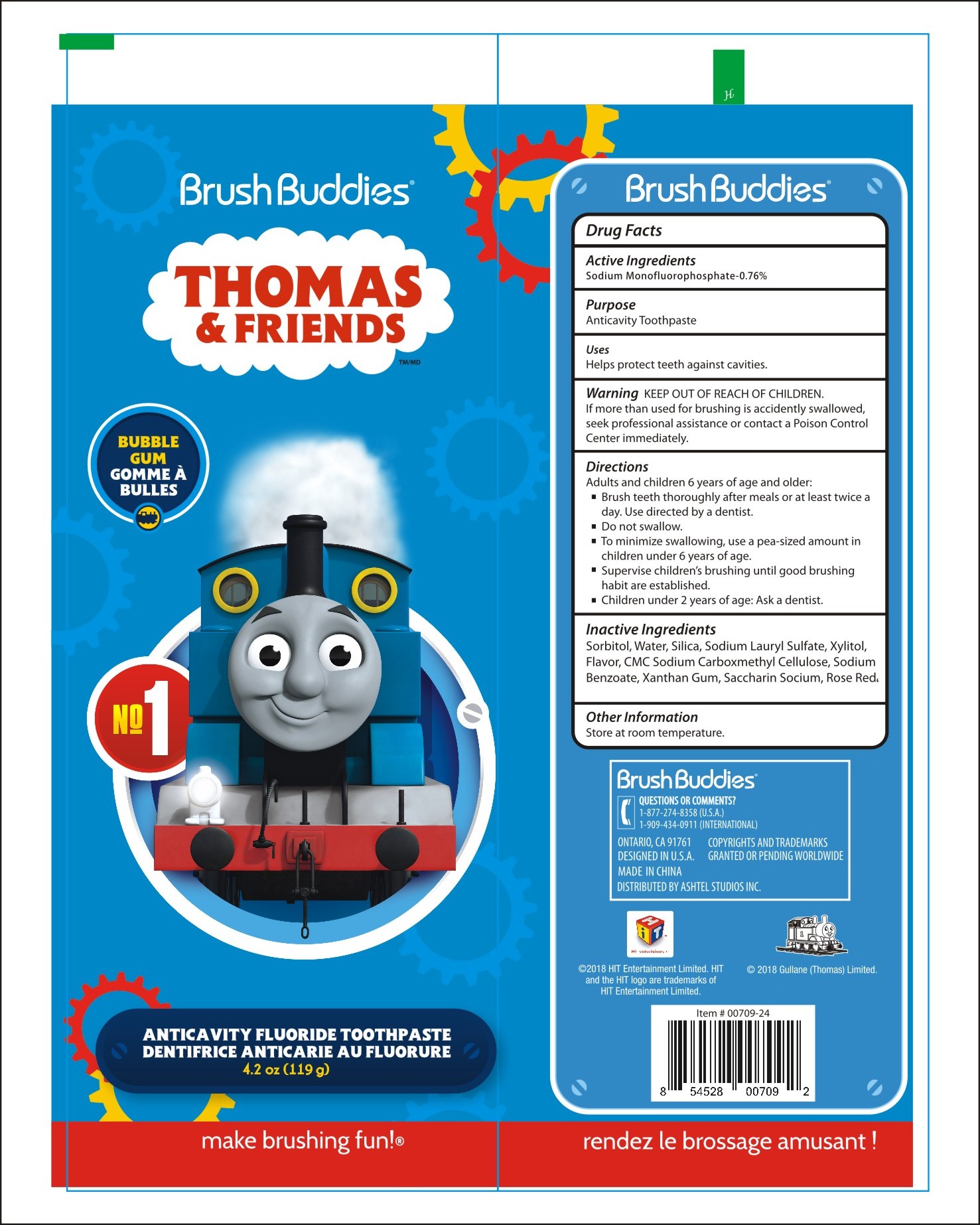 DRUG LABEL: Brushbuddies Thomas Friends Anticavity Fluroride Tooth
NDC: 71106-004 | Form: PASTE, DENTIFRICE
Manufacturer: Foshan Nanhai JiaChun Biology Engineering Co., Ltd
Category: otc | Type: HUMAN OTC DRUG LABEL
Date: 20180802

ACTIVE INGREDIENTS: SODIUM MONOFLUOROPHOSPHATE 0.1 g/100 g
INACTIVE INGREDIENTS: WATER; SORBITOL; XYLITOL; CARBOXYMETHYLCELLULOSE SODIUM; SODIUM BENZOATE; XANTHAN GUM; SACCHARIN SODIUM

Active Ingredient

Sodium Monofluorophosphate 0.76%

Purpose:

Anticavity Toothpaste

INDICATIONS AND USAGE

Uses: Help protect teeth and roots against cavities

Warnings:

If you accidentally swallow more than used for brushing, seek professional help or contact a Poison Control Center immediately

Keep out of reach of children

Directions:

- Adults and children 2 years and older:
- Brush teeth thoroughly after meals or at least twice a day or use as directed by a dentist.
- Do not swallow
- To minimize swallowing use a pea-sized amount in children under 6 years of age,
- Supervise children's brushing untill good habits are established.

Children under 2 years of age:

- Ask a dentist

Inactive Ingredients:

Sorbitor, Water, Silica, Sodium N-Lauroylsarcosinate, Xylitol, Flavor, Sodium Carboxymethylcellulose, Sodium Benzoate, Xanthan Gum, Saccharin Sodium, Rose Red 1